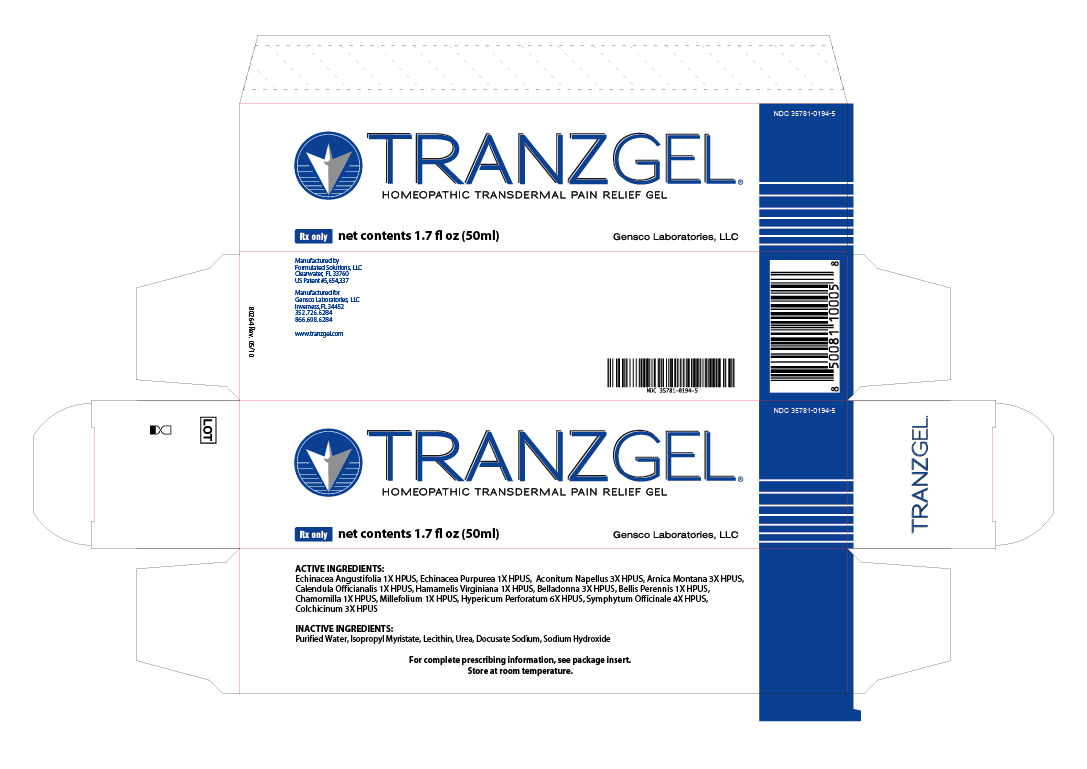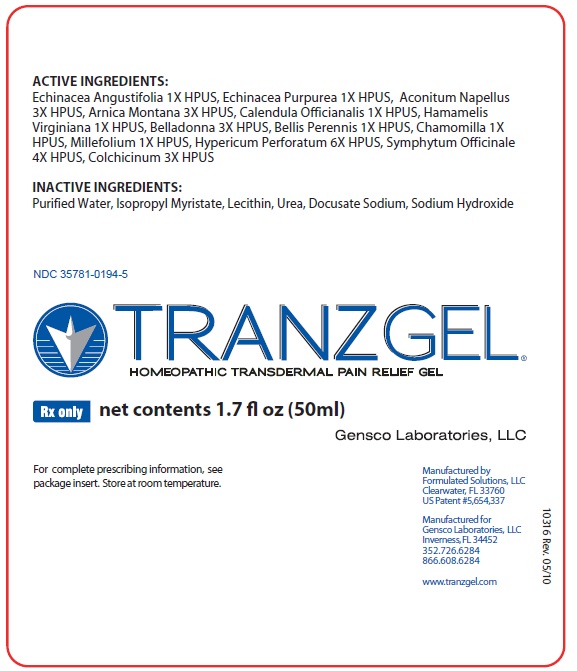 DRUG LABEL: TRANZGEL
NDC: 35781-0194 | Form: GEL
Manufacturer: Gensco Laboratories, LLC
Category: homeopathic | Type: HUMAN PRESCRIPTION DRUG LABEL
Date: 20100929

ACTIVE INGREDIENTS: ECHINACEA ANGUSTIFOLIA 1 [hp_X]/50 mL; ECHINACEA PURPUREA 1 [hp_X]/50 mL; ACONITUM NAPELLUS 3 [hp_X]/50 mL; ARNICA MONTANA 3 [hp_X]/50 mL; CALENDULA OFFICINALIS FLOWERING TOP 1 [hp_X]/50 mL; HAMAMELIS VIRGINIANA ROOT BARK/STEM BARK 1 [hp_X]/50 mL; ATROPA BELLADONNA 3 [hp_X]/50 mL; BELLIS PERENNIS 1 [hp_X]/50 mL; CHAMOMILE 1 [hp_X]/50 mL; ACHILLEA MILLEFOLIUM 1 [hp_X]/50 mL; HYPERICUM OIL 6 [hp_X]/50 mL; COMFREY ROOT 4 [hp_X]/50 mL; COLCHICINE 3 [hp_X]/50 mL
INACTIVE INGREDIENTS: WATER; ISOPROPYL MYRISTATE; LECITHIN, SOYBEAN; UREA; DOCUSATE SODIUM; SODIUM HYDROXIDE

TRANZGEL HOMEOPATHIC TRANSDERMAL PAIN RELIEF GEL

ACTIVE INGREDIENTS:

ECHINACEA ANGUSTIFOLIA 1X HPUS, ECHINACEA PUPUREA 1X HPUS, ACONITUM NAPELLUS 3X HPUS, ARNICA MONTANA 3X HPUS, CALENDULA OFFICIANALIS 1X HPUS, HAMAMELIS VIRGINIANA 1X HPUS, BELLADONNA 3X HPUS, BELLIS PERENNIS 1X HPUS, CHAMOMILLA 1X HPUS, MILLEFOLIUM 1X HPUS, HYPERICUM PERFORATUM 6X HPUS, SYMPHYTUM OFFICINALE 4X HPUS, COLCHICINUM 3X HPUS

INACTIVE INGREDIENTS:

PURIFIED WATER, ISOPROPYL MYRISTATE, LECITHIN, UREA, DOCUSATE SODIUM, SODIUM HYDROXIDE

PACKAGE LABEL

NDC 35781-0194-5

TRANZGEL

HOMEOPATHIC TRANSDERMAL PAIN RELIEF GEL

RX ONLY NET CONTENTS 1.7 FL OZ (50 ML)

GENSCO LABORATORIES, LLC

FOR COMPLETE PRESCRIBING INFORMATION, SEE PACKAGE INSERT. STORE AT ROOM TEMPERATURE.

MANUFACTURED BY FORMULATED SOLUTIONS

CLEARWATER, FL 33760

US PATENT #5,654,337

MANUFACTURED FOR GENSCO LABORATORIES, LLC

INVERNESS, FL 34452

352.726.6284

866.608.6284

WWW.TRANZGEL.COM

PACKAGE LABEL

TRANZ GEL

HOMEOPATHIC TRANSDERMAL PAIN RELIEF GEL

RX ONLY NET CONTENTS 1.7 FL OZ (50 ML)

GENSCO LABORATORIES

MANUFACTURED BY

FORMULATED SOLUTIONS, LLC

CLEARWATER FL 33760

US PATENT #5,654,337

MANUFACTURED BY

GENSCO LABORATORIES, LLC

INVERNESS, FL 34452

352.726.6284

866.608.6284

WWW.TRANZGEL.COM

ACTIVE INGREDIENTS:
ECHINACEA ANGUSTIFOLIA 1X HPUS, ECHINACEA PUPUREA 1X HPUS, ACONITUM NAPELLUS 3X HPUS, ARNICA MONTANA 3X HPUS, CALENDULA OFFICIANALIS 1X HPUS, HAMAMELIS VIRGINIANA 1X HPUS, BELLADONNA 3X HPUS, BELLIS PERENNIS 1X HPUS, CHAMOMILLA 1X HPUS, MILLEFOLIUM 1X HPUS, HYPERICUM PERFORATUM 6X HPUS, SYMPHYTUM OFFICINALE 4X HPUS, COLCHICINUM 3X HPUS

INACTIVE INGREDIENTS:

PURIFIED WATER, ISOPROPYL MYRISTATE, LECITHIN, UREA, DOCUSATE SODIUM, SODIUM HYDROXIDE

For complete prescribing information, see package insert. Store at room temperature.

DESCRIPTION

A homeopathic topical analgesic gel that contains the active ingredients indicated below in the corresponding concentrations.

ACTIVE INGREDIENTS:
50 PARTS EACH: ECHINACEA ANGUSTIFOLIA 1X HPUS, ECHINACEA PUPUREA 1X HPUS, 30 PARTS: ACONITUM NAPELLUS 3X HPUS, 15 PARTS EACH: ARNICA MONTANA 3X HPUS, CALENDULA OFFICIANALIS 1X HPUS, HAMAMELIS VIRGINIANA 1X HPUS, 10 PARTS: BELLADONNA 3X HPUS, 5 PARTS EACH: BELLIS PERENNIS 1X HPUS, CHAMOMILLA 1X HPUS, 3 PARTS MILLEFOLIUM 1X HPUS, 1 PART EACH: HYPERICUM PERFORATUM 6X HPUS, SYMPHYTUM OFFICINALE 4X HPUS, .01 PART COLCHICINUM 3X HPUS

INACTIVE INGREDIENTS:
PURIFIED WATER, ISOPROPYL MYRISTATE, LECITHIN, UREA, DOCUSATE SODIUM, SODIUM HYDROXIDE

Physical Information

A clear amber colored, viscous gel with a slight floral smell.

CLINICAL PHARMACOLOGY

According to traditional homeopathic literature and Material Medica, the following ingredients provide the following attributes:

INGREDIENTS COMMON NAME INDICATIONS

Arnica Montana Mountain arnica Stimulates healing of injured tissues wounds, contusions, hematomas, neuralgia myalgia, analgesia

Calendula Officianalis Calendula Inflammation
Hamamelis Virginiana Witch-hazel Analgesic
Millefolium Yarrow Hematomas
Belladonna Banewort Inflammation locally
Aconitum Napellus Monk's hood Neuralgia, rheumatism hemostasis, analgeisa
Chamomilla Chamomile Inflammation, nausea
Colchicinum Colchicine Inflammation and gout
Symphytum Officinale Comfrey Neuropathy, contusions, tendonitis, arthritis
Bellis Perennis Daisy brusing, edema, arthralgia
Echinacea Angustifolia Narrow leaf cone flower Inflammation, myalgia
Echinacia purpurea purple cone flower Inflammation, myalgia
Hypericum perforatum st. john's wort neuropathic pains

INDICATIONS AND USAGE

The drug is indicated for the relief of symptoms, including pain and inflammation associated with arthritis or trauma (such as sprains, strains, dislocations, repetitive/overuse injuries, traumatic, edema, post surgical edema, hematoma, general swelling of joints and soft tissues) to areas such as hand, wrist elbow, shoulder, neck, back, knees, ankles, feet and toes.

CONTRAINDICATIONS

This drug should not be used by those sensitive to Arnica or any of the other listed ingredients.

WARNINGS AND PRECAUTIONS

For external use only. direct patient not to ingest TRANZEL and to avoid contact with they eyes, mucous membranes, wounds, and damaged skin. If a rash develops, patient should discontinue use until rash clears. After the disappearance of rash, patient can try TRANZGEL again on a test area and monitor the site for additional results. If no rash or redness results, then patient can resume use. However, if the rash persists or redevelops, use should be discontinued.

Direct the patient to keep this product out of reach of children and seek medical help or contact a Poison Control Center immediately if swallowed.

In the homeopathic concentrations used to make TRANZGEL, there are no known or expected interactions with other drugs or laboratory tests. In addition, the homeopathic concentrations used are below any levels with known or suspected toxicities.

OVERDOSAGE

According to toxicology studies, a patient would have to orally ingest a minimum of 22 bottles of TRANZGEL to experience any initial toxic effects.

ADVERSE REACTIONS

Rarely, allergic skin reactions may occur. These effects are transient and will clear after a few days.

DOSAGE AND ADMINISTRATION

Apply a thin layer (1 drop covers an area of skin 2 inches by 2 inches) to the affected area 3-4 times daily and rub in gently. Applications of less than 3-4 times a day will not produce optimum results. Excess drops may be wiped from the area.

HOW SUPPLIED

Package size: 1.7 fl oz (50 ml) airless pump dispensing bottle

US PATENT 5,654,337

NDC 35781-0194-5

PATIENT COUNSELING INFORMATION

STORE AT ROOM TEMPERATURE

Manufactured by

Formulated Solutions, LLC

Clearwater, FL 33760

Manufactured for

Gensco Laboratories, LLC

Inverness, FL 34452

352-726-6284

866-608-6284

www.tranzgel.com